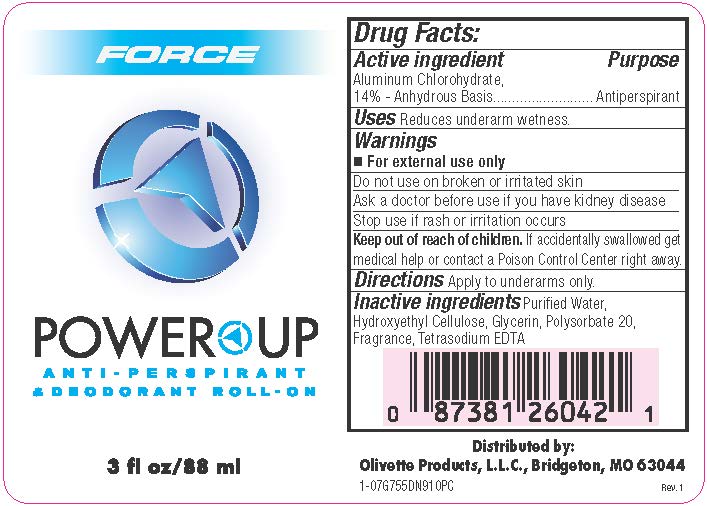 DRUG LABEL: Roll On Anti-Perspirant Deodorant
NDC: 51870-001 | Form: SOLUTION
Manufacturer: Keefe Group
Category: otc | Type: HUMAN OTC DRUG LABEL
Date: 20241115

ACTIVE INGREDIENTS: ALUMINUM CHLOROHYDRATE 14 g/100 mL
INACTIVE INGREDIENTS: WATER; HYDROXYETHYL CELLULOSE, UNSPECIFIED; GLYCERIN; POLYSORBATE 20; EDETATE SODIUM

14% Roll On Anti-Perspirant Deodorant

Drug Facts

Active ingredient

Aluminum Chlorohydrate, 14% – Anhydrous Basis

Purpose

Antiperspirant

Use

Reduces underarm wetness.

Warnings

For external use only.

Keep out of reach of children.

Do not use on broken skin.

Stop use if rash or irritation occurs.

Ask a doctor before use if you havekidney disease. If swallowed, get medical help or contact a Poison Control Center immediately. Use only as directed.

Directions

Apply to underarms only.

Inactive ingredients

Purified Water, Hydroxyethylcellulose, Glycerin, Polysorbate 20, Fragrance, Tetrasodium EDTA

Distributed by:
Olivette Products, L.L.C., Bridgeton, MO 63044

PRINCIPAL DISPLAY PANEL - 88 ml Bottle Label

FORCE

POWER UP
ANTI-PERSPIRANT
& DEODORANT ROLL-ON

3 fl oz/88 ml